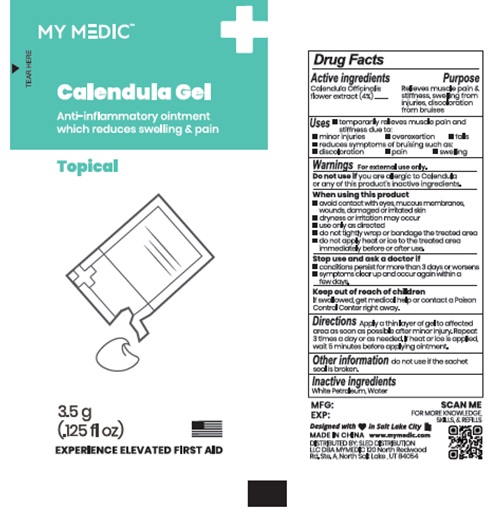 DRUG LABEL: MY MEDIC CALENDULA
NDC: 81417-007 | Form: GEL
Manufacturer: Sled Distribution, LLC
Category: homeopathic | Type: HUMAN OTC DRUG LABEL
Date: 20240115

ACTIVE INGREDIENTS: CALENDULA OFFICINALIS FLOWER 4 g/100 g
INACTIVE INGREDIENTS: WATER; WHITE PETROLATUM

81417-007 MY MEDIC CALENDULA GEL

Active ingredients

Calendula Officinalis Flower Extract (4%)

Purpose Section

Relieves muscle pain and stiffness, swelling from injuries, discoloration from bruises.

Uses

temporarily relieve muscle pain and stiffness due to:

- minor infuries
- overexertion
- falls
- reduces symptoms of bruising such as
- discoloration
- pain
- swelling

Warnings

For external use only.

Do not use if you are allergic to Calendula or any of this product's inactive ingredients.

When using this product

- avoid contact with eyes, mucous membranes, wounds, damaged or irritated skin
- dryness or irritation may occur
- use only as directed
- do not tightly wrap or bandage the treated area
- do not apply heat or ice to the treated area immediately before or after use.

Stop use and ask a doctor if

- conditions persist for more than3 days or worsens
- symptoms clear up and occur again within a few days

Keep out of reach of children

If swallowed, get medical help or contact a Poison Control Center right away.

Directions

Apply a thin layer of gel to affected area as soon as possible after minor injury. Repeat 3 times a day or as needed. lf heat or ice is applied, wait 5 minutes before applying ointment.

Other information

do not use if the sachet seal is broken.

Inactive ingredients

White Petroleum, Water